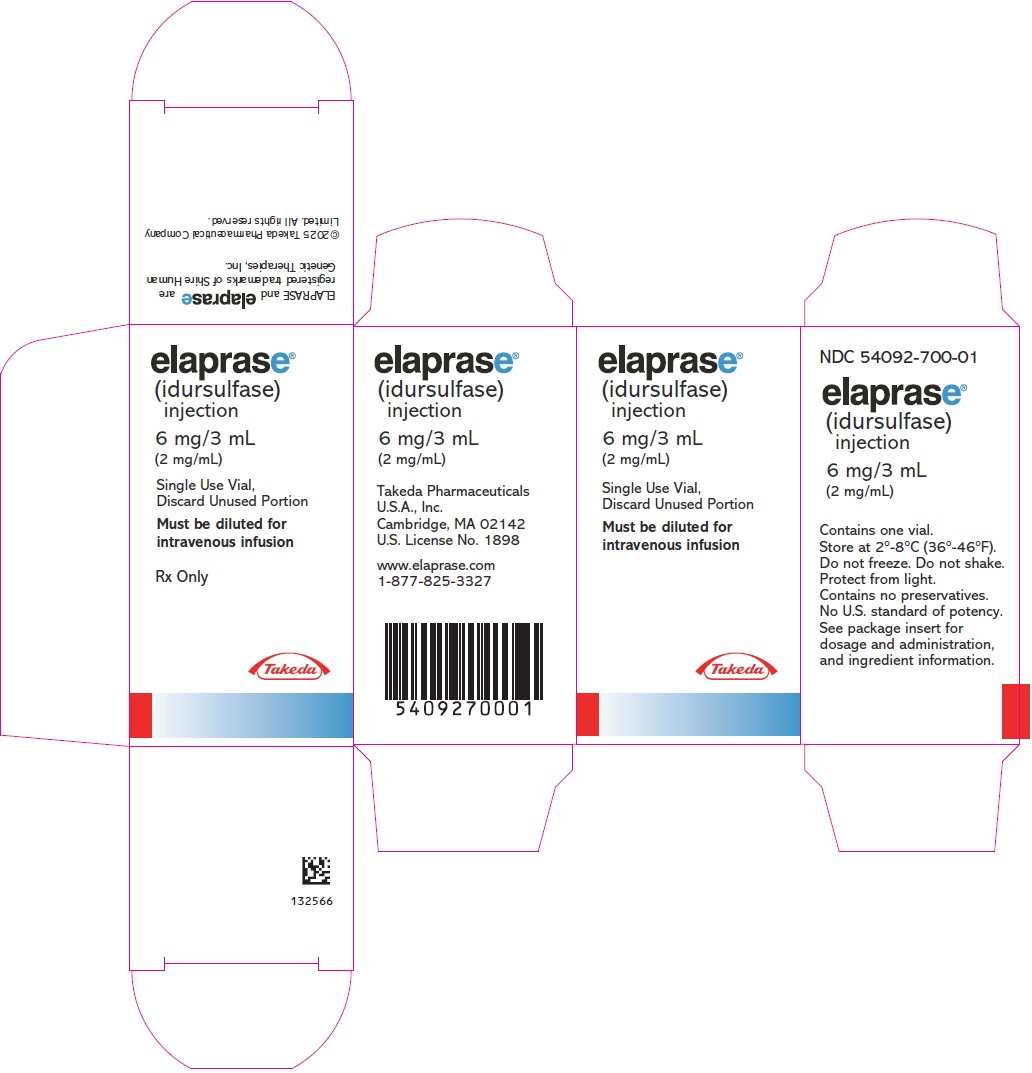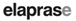 DRUG LABEL: ELAPRASE
NDC: 54092-700 | Form: SOLUTION, CONCENTRATE
Manufacturer: Takeda Pharmaceuticals America, Inc.
Category: prescription | Type: HUMAN PRESCRIPTION DRUG LABEL
Date: 20250415

ACTIVE INGREDIENTS: idursulfase 6 mg/3 mL
INACTIVE INGREDIENTS: sodium chloride 24 mg/3 mL; sodium phosphate, monobasic, monohydrate 6.75 mg/3 mL; sodium phosphate, dibasic, heptahydrate 2.97 mg/3 mL; polysorbate 20 0.66 mg/3 mL

HIGHLIGHTS OF PRESCRIBING INFORMATION

These highlights do not include all the information needed to use ELAPRASE safely and effectively. See full prescribing information for ELAPRASE.
ELAPRASE® (idursulfase) injection, for intravenous use
Initial U.S. Approval: 2006

WARNING: RISK OF ANAPHYLAXIS

See full prescribing information for complete boxed warning.

Life-threatening anaphylactic reactions, presenting as respiratory distress, hypoxia, hypotension, urticaria and/or angioedema of throat or tongue have occurred in some patients during and up to 24 hours after ELAPRASE infusions. Closely observe patients during and after ELAPRASE administration and be prepared to manage anaphylaxis. Inform patients of the signs and symptoms of anaphylaxis and have them seek immediate medical care should symptoms occur. Patients with compromised respiratory function or acute respiratory disease may be at risk of serious acute exacerbation of their respiratory compromise due to hypersensitivity reactions and require additional monitoring. (5.1, 5.3, 6)

1 INDICATIONS AND USAGE

ELAPRASE is a hydrolytic lysosomal glycosaminoglycan (GAG)-specific enzyme indicated for patients with Hunter syndrome (Mucopolysaccharidosis II, MPS II). ELAPRASE has been shown to improve walking capacity in patients 5 years and older. In patients 16 months to 5 years of age, no data are available to demonstrate improvement in disease-related symptoms or long term clinical outcome; however, treatment with ELAPRASE has reduced spleen volume similarly to that of adults and children 5 years of age and older. The safety and efficacy of ELAPRASE have not been established in pediatric patients less than 16 months of age (1).

2 DOSAGE AND ADMINISTRATION

The recommended dosage is 0.5 mg per kg of body weight administered once every week as an intravenous infusion (2).

3 DOSAGE FORMS AND STRENGTHS

Injection: 6 mg/3 mL (2 mg/mL) in single-use vial (3)

4 CONTRAINDICATIONS

None. (4)

5 WARNINGS AND PRECAUTIONS

- Hypersensitivity Reactions Including Anaphylaxis: Ensure that personnel administering product are adequately trained in cardio-pulmonary resuscitative measures and have ready access to emergency medical services (EMS) (5.1).
- Risk of Hypersensitivity, Serious Adverse Reactions, and Antibody Development in Hunter Syndrome Patients with Severe Genetic Mutations: Hunter syndrome patients aged 7 years and younger with complete gene deletion, large gene rearrangement, nonsense, frameshift, or splice site mutations experienced a higher incidence of hypersensitivity reactions, serious adverse reactions, and anti-idursulfase antibody development (5.2).
- Risk of Acute Respiratory Complications: Patients with compromised respiratory function or acute febrile or respiratory illness may be at higher risk of life-threatening complications from hypersensitivity reactions. Careful consideration should be given to the patient's clinical status prior to administration of ELAPRASE and consider delaying the ELAPRASE infusion (5.3).

6 ADVERSE REACTIONS

The most common adverse reactions occurring in at least three patients (≥9%) aged five years and older were headache, pruritus, musculoskeletal pain, urticaria, diarrhea, and cough. The most common adverse reactions occurring in at least three patients (≥10%) aged seven years and younger were pyrexia, rash, vomiting, and urticaria. In all clinical trials, the most common adverse reactions requiring medical intervention were hypersensitivity reactions, and included rash, urticaria, pruritus, flushing, pyrexia, and headache (6.1).

To report SUSPECTED ADVERSE REACTIONS, contact Takeda Pharmaceuticals U.S.A., Inc. at 1-877-TAKEDA-7 (1-877-825-3327) or FDA at 1-800-FDA-1088 or www.fda.gov/medwatch.

FULL PRESCRIBING INFORMATION

WARNING: RISK OF ANAPHYLAXIS

Life-threatening anaphylactic reactions have occurred in some patients during and up to 24 hours after ELAPRASE infusions. Anaphylaxis, presenting as respiratory distress, hypoxia, hypotension, urticaria and/or angioedema of throat or tongue have been reported to occur during and after ELAPRASE infusions, regardless of duration of the course of treatment. Closely observe patients during and after ELAPRASE administration and be prepared to manage anaphylaxis. Inform patients of the signs and symptoms of anaphylaxis and have them seek immediate medical care should symptoms occur. Patients with compromised respiratory function or acute respiratory disease may be at risk of serious acute exacerbation of their respiratory compromise due to hypersensitivity reactions and require additional monitoring [see Warnings and Precautions (5.1, 5.3) and Adverse Reactions (6)].

1 INDICATIONS AND USAGE

ELAPRASE is indicated for patients with Hunter syndrome (Mucopolysaccharidosis II, MPS II). ELAPRASE has been shown to improve walking capacity in patients 5 years and older.

In patients 16 months to 5 years of age, no data are available to demonstrate improvement in disease-related symptoms or long term clinical outcome; however, treatment with ELAPRASE has reduced spleen volume similarly to that of adults and children 5 years of age and older.

The safety and efficacy of ELAPRASE have not been established in pediatric patients less than 16 months of age [see Use in Specific Populations (8.4)].

2 DOSAGE AND ADMINISTRATION

2.1 Recommended Dose

The recommended dosage regimen of ELAPRASE is 0.5 mg per kg of body weight administered once weekly as an intravenous infusion.

Parenteral drug products should be inspected visually for particulate matter and discoloration prior to administration, whenever solution and container permit.

2.2 Preparation Instructions

Prepare and use ELAPRASE according to the following steps using aseptic technique:

1. Determine the total volume of ELAPRASE to be administered and the number of vials needed based on the patient's weight and the recommended dose of 0.5 mg/kg.
  Patient's weight (kg) × 0.5 mg per kg of ELAPRASE ÷ 2 mg per mL =
  Total mL of ELAPRASE
  Total mL of ELAPRASE ÷ 3 mL per vial = Total number of vials
  Round up to the next whole vial to determine the total number of vials needed. Remove the required number of vials from the refrigerator to allow them to reach room temperature.
2. Before withdrawing the ELAPRASE solution from the vial, visually inspect each vial for particulate matter and discoloration. The ELAPRASE solution should be clear to slightly opalescent and colorless. Do not use if the solution is discolored or if there is particulate matter in the solution. Do not shake the ELAPRASE solution.
3. Withdraw the calculated volume of ELAPRASE from the appropriate number of vials.
4. Add the calculated volume of ELAPRASE solution to a 100 mL bag of 0.9% Sodium Chloride Injection, USP for intravenous infusion.
5. Mix gently. Do not shake the solution.

2.3 Administration Instructions

Administer the diluted ELAPRASE solution to patients using a low-protein-binding infusion set equipped with a low-protein-binding 0.2 micrometer (µm) in-line filter.

The total volume of infusion should be administered over a period of 3 hours, which may be gradually reduced to 1 hour if no hypersensitivity reactions are observed. Patients may require longer infusion times if hypersensitivity reactions occur; however, infusion times should not exceed 8 hours. The initial infusion rate should be 8 mL per hour for the first 15 minutes. If the infusion is well tolerated, the rate of infusion may be increased by 8 mL per hour increments every 15 minutes. The infusion rate should not exceed 100 mL per hour. The infusion rate may be slowed, temporarily stopped, or discontinued for that visit in the event of hypersensitivity reactions [see Warnings and Precautions (5.1)]. ELAPRASE should not be infused with other products in the infusion tubing.

2.4 Storage and Stability

ELAPRASE does not contain preservatives; therefore, after dilution with saline, the infusion bags should be used immediately. If immediate use is not possible, the diluted solution should be stored refrigerated at 2°C to 8°C (36°F to 46 °F) for up to 24 hours. Other than during infusion, do not store the diluted ELAPRASE solution at room temperature. Any unused product or waste material should be discarded and disposed of in accordance with local requirements.

3 DOSAGE FORMS AND STRENGTHS

Injection: 6 mg/3 mL (2 mg/mL) in single-use vials

4 CONTRAINDICATIONS

None.

5 WARNINGS AND PRECAUTIONS

5.1 Hypersensitivity Reactions Including Anaphylaxis

Serious hypersensitivity reactions, including anaphylaxis, have occurred during and up to 24 hours after infusion. Some of these reactions were life-threatening and included respiratory distress, hypoxia, hypotension, urticaria, and angioedema of the throat or tongue, regardless of duration of the course of treatment.

If anaphylactic or other acute reactions occur, immediately discontinue the infusion of ELAPRASE and initiate appropriate medical treatment. When severe reactions have occurred during clinical trials, subsequent infusions were managed with antihistamine and/or corticosteroids prior to or during infusions, a slower rate of ELAPRASE infusion, and/or early discontinuation of the ELAPRASE infusion [see Adverse Reactions (6)].

In clinical trials with ELAPRASE, 16 of 108 (15%) patients experienced hypersensitivity reactions during 26 of 8,274 infusions (0.3%) that involved adverse events in at least two of the following three body systems: cutaneous, respiratory, or cardiovascular. Of these 16 patients, 11 experienced anaphylactic reactions during 19 of 8,274 infusions (0.2%) with symptoms of bronchospasm, cyanosis, dyspnea, erythema, edema (facial and peripheral), flushing, rash, respiratory distress, urticaria, vomiting, and wheezing.

In postmarketing reports, patients receiving ELAPRASE experienced anaphylactic reactions up to several years after initiating treatment. Some patients were reported to have repeated anaphylactic events over a two- to four-month time period. Medical management included treatment with antihistamines, inhaled beta-adrenergic agonists, corticosteroids, oxygen, and vasopressors. Treatment was discontinued for some patients, while others continued treatment with premedication and a slower infusion rate.

Due to the potential for severe reactions, appropriate medical support should be readily available when ELAPRASE is administered. Observe patients closely for an appropriate period of time after administration of ELAPRASE, taking into account the time to onset of anaphylaxis seen in premarketing clinical trials and postmarketing reports. Inform patients of the signs and symptoms of anaphylaxis and instruct them to seek immediate medical care should signs and symptoms occur.

5.2 Risk of Hypersensitivity, Serious Adverse Reactions, and Antibody Development in Hunter Syndrome Patients with Severe Genetic Mutations

In the clinical trial of Hunter syndrome patients aged 7 years and younger, patients with complete gene deletion, large gene rearrangement, nonsense, frameshift, or splice site mutations experienced a higher incidence of hypersensitivity reactions, serious adverse reactions, and anti-idursulfase antibody development than Hunter syndrome patients with missense mutations. Eleven of 15 (73%) patients with complete gene deletion, large gene rearrangement, nonsense, frameshift, or splice site mutations and five of 12 (42%) patients with missense mutations experienced hypersensitivity reactions. Nine of 15 (60%) patients with complete gene deletion, large gene rearrangement, nonsense, frameshift, or splice site mutations and two of 12 (17%) patients with missense mutations had serious adverse reactions. All 15 patients with complete gene deletion, large gene rearrangement, nonsense, frameshift, or splice site mutations developed anti-idursulfase (ELAPRASE) antibodies, compared to only 3 patients with missense mutations (Table 2). Thirteen patients with these mutations developed neutralizing antibodies, which interfere with ELAPRASE uptake into the cell or ELAPRASE enzyme activity, compared to only one patient with missense mutation [see Warnings and Precautions (5.1), Adverse Reactions (6.1, 6.2), and Use in Specific Populations (8.4)].

5.3 Risk of Acute Respiratory Complications

Patients with compromised respiratory function or acute febrile or respiratory illness at the time of ELAPRASE infusion may be at higher risk of life-threatening complications from hypersensitivity reactions. Careful consideration should be given to the patient's clinical status prior to administration of ELAPRASE and consider delaying the ELAPRASE infusion. One patient with a tracheostomy, severe airway disease, and acute febrile illness experienced respiratory distress, hypoxia, cyanosis, and seizure with a loss of consciousness during ELAPRASE infusion.

5.4 Risk of Acute Cardiorespiratory Failure

Caution should be exercised when administering ELAPRASE to patients susceptible to fluid overload, or patients with acute underlying respiratory illness or compromised cardiac and/or respiratory function for whom fluid restriction is indicated. These patients may be at risk of serious exacerbation of their cardiac or respiratory status during infusions. Appropriate medical support and monitoring measures should be readily available during ELAPRASE infusion, and some patients may require prolonged observation times that should be based on the individual needs of the patient [see Adverse Reactions (6.1, 6.3)].

6 ADVERSE REACTIONS

6.1 Clinical Trials Experience

Because clinical trials are conducted under widely varying conditions, adverse reaction rates observed in the clinical trials of a drug cannot be directly compared to rates in the clinical trials of another drug and may not reflect the rates observed in practice.

The following serious adverse reactions are described below and elsewhere in the labeling:

- Hypersensitivity Reactions Including Anaphylaxis [see Warnings and Precautions (5.1)]

In clinical trials, the most common adverse reactions (>10%) following ELAPRASE treatment were hypersensitivity reactions, and included rash, urticaria, pruritus, flushing, pyrexia, and headache. Most hypersensitivity reactions requiring intervention were ameliorated with slowing of the infusion rate, temporarily stopping the infusion, with or without administering additional treatments including antihistamines, corticosteroids, or both prior to or during infusions.

In clinical trials, the most frequent serious adverse reactions following ELAPRASE treatment were hypoxic episodes. Other notable serious adverse reactions that occurred in the ELAPRASE-treated patients but not in the placebo-treated patients included one case each of: cardiac arrhythmia, pulmonary embolism, cyanosis, respiratory failure, infection, and arthralgia.

Clinical Trials in Patients 5 Years and Older

A 53-week, double-blind, placebo-controlled clinical trial of ELAPRASE was conducted in 96 male patients with Hunter syndrome, ages 5-31 years old. Of the 96 patients, 83% were White, non-Hispanic. Patients were randomized to three treatment groups, each with 32 patients: ELAPRASE 0.5 mg/kg once weekly, ELAPRASE 0.5 mg/kg every other week, or placebo. Hypersensitivity reactions were reported in 69% (22 of 32) of patients who received once-weekly treatment of ELAPRASE.

Table 1 summarizes the adverse reactions that occurred in at least 9% of patients (≥3 patients) in the ELAPRASE 0.5 mg/kg once weekly group and with a higher incidence than in the placebo group.

Table 1. Adverse Reactions that Occurred in the Placebo-Controlled Trial in At Least 9% of Patients in the ELAPRASE 0.5 mg/kg Once Weekly Group and with a Higher Incidence than in the Placebo Group (5 Years and Older)
System Organ Class Adverse Reaction | ELAPRASE (0.5 mg/kg weekly) N=32 n (%) | Placebo N=32 n (%)
Gastrointestinal disorder
Diarrhea | 3 (9%) | 1 (3%)
Musculoskeletal and Connective Tissue Disorders
Musculoskeletal Pain | 4 (13%) | 1 (3%)
Nervous system disorders
Headache | 9 (28%) | 8 (25%)
Respiratory, thoracic and mediastinal disorders
Cough | 3 (9%) | 1 (3%)
Skin and subcutaneous tissue disorders
Pruritus | 8 (25%) | 3 (9%)
Urticaria | 5 (16%) | 0 (0%)

Additional adverse reactions that occurred in at least 9% of patients (≥3 patients) in the ELAPRASE 0.5 mg/kg every other week group and with a higher incidence than in the placebo group included: rash (19%), flushing (16%), fatigue (13%), tachycardia (9%), and chills (9%).

Extension Trial

An open-label extension trial was conducted in patients who completed the placebo-controlled trial. Ninety-four of the 96 patients who were enrolled in the placebo-controlled trial consented to participate in the extension trial. All 94 patients received ELAPRASE 0.5 mg/kg once weekly for 24 months. No new serious adverse reactions were reported. Approximately half (53%) of patients experienced hypersensitivity reactions during the 24-month extension trial. In addition to the adverse reactions listed in Table 1, common hypersensitivity reactions occurring in at least 5% of patients (≥5 patients) in the extension trial included: rash (23%), pyrexia (9%), flushing (7%), erythema (7%), nausea (5%), dizziness (5%), vomiting (5%), and hypotension (5%).

Clinical Trial in Patients 7 Years and Younger

A 53-week, open-label, single-arm, safety trial of once weekly ELAPRASE 0.5 mg/kg treatment was conducted in patients with Hunter syndrome, ages 16 months to 4 years old (n=20) and ages 5 to 7.5 years old (n=8) at enrollment. Patients experienced similar adverse reactions as those observed in clinical trials in patients 5 years and older, with the most common adverse reactions following ELAPRASE treatment being hypersensitivity reactions (57%). A higher incidence of the following common hypersensitivity reactions were reported in this younger age group: pyrexia (36%), rash (32%), and vomiting (14%). The most common serious adverse reactions occurring in at least 10% of patients (≥3 patients) included: bronchopneumonia/pneumonia (18%), ear infection (11%), and pyrexia (11%).

Twenty-seven patients had results of genotype analysis: 15 patients had complete gene deletion, large gene rearrangement, nonsense, frameshift, or splice site mutations and 12 patients had missense mutations.

Safety results demonstrated that patients with complete gene deletion, large gene rearrangement, nonsense, frameshift, or splice site mutations are more likely to experience hypersensitivity reactions and have serious adverse reactions following ELAPRASE administration, compared to patients with missense mutations. Table 2 summarizes these findings.

Table 2. Impact of Antibody Status and Genetic Mutations on Occurrence of Serious Adverse Reactions and Hypersensitivity in Patients 7 Years and Younger Treated with ELAPRASE
 |  |  |  | Anti-idursulfase antibodies (Ab) |  | Anti-idursulfase neutralizing antibodies (Nab)
 |  |  | Total | Positive | Negative | Positive | Negative
Antibody Status Reported (patients) |  |  | 28 | 19 | 9 | 15 | 13
Serious Adverse Reactions [Serious adverse reactions included: bronchopneumonia/pneumonia, ear infection, and pyrexia [see Adverse Reactions (6.1)].] (patients) |  |  | 13 | 11 | 2 | 9 | 4
Hypersensitivity (patients) |  |  | 16 | 12 | 4 | 10 | 6
Patients with genotype data |  |  | 27
M U T A T I O N S | Missense Mutation (n=12) | Antibody status | 12 | 3 | 9 | 1 | 11
M U T A T I O N S | Missense Mutation (n=12) | Serious Adverse Reactions | 2 | 0 | 2 | 0 | 2
M U T A T I O N S | Missense Mutation (n=12) | Hypersensitivity Reactions | 5 | 1 | 4 | 0 | 5
M U T A T I O N S | Complete Gene Deletion, Large Gene Rearrangement, Nonsense, Frameshift, Splice Site Mutations (n=15) | Antibody Status | 15 | 15 | 0 | 13 | 2
M U T A T I O N S | Complete Gene Deletion, Large Gene Rearrangement, Nonsense, Frameshift, Splice Site Mutations (n=15) | Serious Adverse Reactions | 9 | 9 | 0 | 7 | 2
M U T A T I O N S | Complete Gene Deletion, Large Gene Rearrangement, Nonsense, Frameshift, Splice Site Mutations (n=15) | Hypersensitivity Reactions | 11 | 11 | 0 | 10 | 1

6.2 Immunogenicity

Clinical Trials in Patients 5 Years and Older

As with all therapeutic proteins, there is potential for immunogenicity. In clinical trials in patients 5 years and older, 63 of the 64 patients treated with ELAPRASE 0.5 mg/kg once weekly or placebo for 53 weeks, followed by ELAPRASE 0.5 mg/kg once weekly in the extension trial, had immunogenicity data available for analysis. Of the 63 patients, 32 (51%) patients tested positive for anti-idursulfase IgG antibodies (Ab) at least one time (Table 2). Of the 32 Ab-positive patients, 23 (72%) tested positive for Ab at three or more different time points (persistent Ab). The incidence of hypersensitivity reactions was higher in patients who tested positive for Ab than those who tested negative.

Thirteen of 32 (41%) Ab-positive patients also tested positive for antibodies that neutralize idursulfase uptake into cells (uptake neutralizing antibodies, uptake NAb) or enzymatic activity (activity NAb) at least one time, and 8 (25%) of Ab-positive patients had persistent NAb. There was no clear relationship between the presence of either Ab or NAb and therapeutic response.

Clinical Trial in Patients 7 Years and Younger

In the clinical trial in patients 7 years and younger, 19 of 28 (68%) patients treated with ELAPRASE 0.5 mg/kg once weekly tested Ab-positive. Of the 19 Ab-positive patients, 16 (84%) tested positive for Ab at three or more different time points (persistent Ab). In addition, 15 of 19 (79%) Ab-positive patients tested positive for NAb, with 14 of 15 (93%) NAb-positive patients having persistent NAb.

All 15 patients with complete gene deletion, large gene rearrangement, nonsense, frameshift, or splice site mutations tested positive for Ab (Table 2). Of these 15 patients, neutralizing antibodies were observed in 13 (87%) patients. The NAbs in these patients developed earlier (most reported to be positive at Week 9 rather than at Week 27, as reported in clinical trials in patients older than 5 years of age) and were associated with higher titers and greater in vitro neutralizing activity than in patients older than 5 years of age. The presence of Ab was associated with reduced systemic idursulfase exposure [see Clinical Pharmacology (12.3)].

The immunogenicity data reflect the percentage of patients whose test results were positive for antibodies to idursulfase in specific assays and are highly dependent on the sensitivity and specificity of these assays. The observed incidence of positive antibody in an assay may be influenced by several factors, including sample handling, timing of sample collection, concomitant medication, and underlying disease. For these reasons, comparison of the incidence of antibodies to idursulfase with the incidence of antibodies to other products may be misleading.

6.3 Postmarketing Experience

The following adverse reactions have been identified during post-approval use of ELAPRASE. Because these reactions are reported voluntarily from a population of uncertain size, it is not always possible to reliably estimate their frequency or establish a causal relationship to drug exposure.

In post-marketing experience, late-emergent symptoms and signs of anaphylactic reactions have occurred up to 24 hours after initial treatment and recovery from an initial anaphylactic reaction. In addition, patients experienced repeated anaphylaxis over a two- to four-month period, up to several years after initiating ELAPRASE treatment [see Warnings and Precautions (5.1)].

A seven year-old male patient with Hunter syndrome, who received ELAPRASE at twice the recommended dosage (1 mg/kg weekly) for 1.5 years, experienced two anaphylactic events after 4.5 years of treatment. Treatment has been withdrawn [see Overdosage (10)].

Serious adverse reactions that resulted in death included cardiorespiratory arrest, respiratory failure, respiratory distress, cardiac failure, and pneumonia.

8 USE IN SPECIFIC POPULATIONS

8.1 Pregnancy

Risk Summary

There are no adequate and well-controlled studies with ELAPRASE use in pregnant women. Available data from a small number of postmarketing cases with ELAPRASE use in pregnancy are insufficient to inform drug-associated risks for major birth defects, miscarriage, or adverse maternal or fetal outcomes. In an animal reproduction study, no evidence of adverse effects on pre- and post-natal development was observed with twice weekly intravenous administration of idursulfase to pregnant rats from gestation day 6 through lactation day 19 at about 4 times the recommended human weekly dose of 0.5 mg/kg based on body surface area (see Data).

The estimated background risk of major birth defects and miscarriage for the indicated population is unknown. All pregnancies have a background risk of birth defect, loss, or other adverse outcomes. In the U.S. general population, the estimated background risk of major birth defects and miscarriage in clinically recognized pregnancies is 2% to 4% and 15% to 20%, respectively.

Data

Animal Data

In a pre- and post-natal development study, idursulfase was administered to pregnant rats twice weekly, intravenously, from gestation day 6 through lactation day 19. No significant adverse effects on pre- and post-natal development of the offspring were observed at twice weekly intravenous doses up to 12.5 mg/kg (about 4 times the recommended human weekly dose of 0.5 mg/kg based on body surface area).

8.2 Lactation

Risk Summary

There are no data on the presence of idursulfase in human milk, the effects on the breastfed infant, or the effects on milk production. Idursulfase was excreted in breast milk of lactating rats (see Data). When a drug is present in animal milk, it is likely that the drug will be present in human milk. The developmental and health benefits of breastfeeding should be considered along with the mother's clinical need for ELAPRASE and any potential adverse effects on the breastfed child from ELAPRASE or from the underlying maternal condition.

Data

Idursulfase was excreted in breast milk of lactating rats at a concentration higher (4- to 5-fold) than the maximum blood concentration, when administered as a single intravenous dose up to 2.5 mg/kg. The concentration of drug in animal milk does not necessarily predict the concentration of drug in human milk.

8.4 Pediatric Use

Clinical trials with ELAPRASE were conducted in 96 patients with Hunter syndrome, ages 5 to 31 years old, with the majority of the patients in the pediatric age group (median age 15 years old). In addition, an open-label, uncontrolled clinical trial was conducted in 28 patients with Hunter syndrome, ages 16 months to 7.5 years old. Patients 16 months to 5 years of age demonstrated reduction in spleen volume that was similar to that of adults and children 5 years and older. However, there are no data to support improvement in disease-related symptoms or long term clinical outcome in patients 16 months to 5 years of age [see Clinical Studies (14)].

The safety and effectiveness of ELAPRASE have not been established in pediatric patients less than 16 months of age.

8.5 Geriatric Use

Clinical studies of ELAPRASE did not include patients older than 31 years of age. It is not known whether older patients respond differently from younger patients.

10 OVERDOSAGE

One patient with Hunter syndrome, who received ELAPRASE at twice the recommended dosage for one and a half years, experienced two anaphylactic reactions over a 3-month period 4.5 years after initiating ELAPRASE treatment.

11 DESCRIPTION

ELAPRASE is a formulation of idursulfase, a purified form of human iduronate-2-sulfatase, a lysosomal enzyme. Idursulfase is produced by recombinant DNA technology in a human cell line. Idursulfase is an enzyme that hydrolyzes the 2-sulfate esters of terminal iduronate sulfate residues from the glycosaminoglycans dermatan sulfate and heparan sulfate in the lysosomes of various cell types.

Idursulfase is a 525-amino acid glycoprotein with a molecular weight of approximately 76 kilodaltons. The enzyme contains eight asparagine-linked glycosylation sites occupied by complex oligosaccharide structures. The enzyme activity of idursulfase is dependent on the post-translational modification of a specific cysteine to formylglycine. Idursulfase has a specific activity ranging from 46 to 74 units/mg of protein (one unit is defined as the amount of enzyme required to hydrolyze 1 micromole of heparin disaccharide substrate per hour under the specified assay conditions).

ELAPRASE is administered as an intravenous infusion and supplied as a sterile, nonpyrogenic clear to slightly opalescent, colorless solution that must be diluted prior to administration in 0.9% Sodium Chloride Injection, USP. Each vial contains an extractable volume of 3 mL with an idursulfase concentration of 2 mg/mL at a pH of approximately 6. Each vial contains 6 mg idursulfase, sodium chloride (24 mg), sodium phosphate monobasic monohydrate (6.75 mg), sodium phosphate dibasic heptahydrate (2.97 mg), and polysorbate 20 (0.66 mg). ELAPRASE does not contain preservatives. Each vial is for single use only.

12 CLINICAL PHARMACOLOGY

12.1 Mechanism of Action

Hunter syndrome (Mucopolysaccharidosis II, MPS II) is an X-linked recessive disease caused by insufficient levels of the lysosomal enzyme iduronate-2-sulfatase. This enzyme cleaves the terminal 2-O-sulfate moieties from the glycosaminoglycans (GAG) dermatan sulfate and heparan sulfate. Due to the missing or defective iduronate-2-sulfatase enzyme in patients with Hunter syndrome, GAG progressively accumulate in the lysosomes of a variety of cells, leading to cellular engorgement, organomegaly, tissue destruction, and organ system dysfunction.

ELAPRASE is intended to provide exogenous enzyme for uptake into cellular lysosomes. Mannose-6-phosphate (M6P) residues on the oligosaccharide chains allow binding of the enzyme to the M6P receptors on the cell surface, leading to cellular internalization of the enzyme, targeting to intracellular lysosomes and subsequent catabolism of accumulated GAG.

12.2 Pharmacodynamics

Decreases in urinary GAG levels were observed following treatment with ELAPRASE. The responsiveness of urinary GAG to dosage alterations of ELAPRASE is unknown, and the relationship of urinary GAG to other measures of clinical response has not been established. Patients who tested positive for anti-idursulfase antibodies (Ab) experienced a less pronounced decrease in urinary GAG levels [see Adverse Reactions (6.2) and Clinical Studies (14.1, 14.2)].

12.3 Pharmacokinetics

Clinical Trials in Patients 5 Years and Older

The pharmacokinetic characteristics of idursulfase were evaluated in 59 patients with Hunter syndrome. The serum concentration of idursulfase was quantified using an antigen-specific ELISA assay. The area under the concentration-time curve (AUC) increased in a greater than dose proportional manner as the dose increased from 0.15 mg/kg to 1.5 mg/kg following a single 1-hour infusion of ELAPRASE. The pharmacokinetic parameters at the recommended dose regimen (0.5 mg/kg ELAPRASE administered weekly as a 3-hour infusion) were determined at Week 1 and Week 27 in 10 patients 7.7 to 27 years of age (Table 3). There were no apparent differences in PK parameter values between Week 1 and Week 27 regardless of the antibody status in these patients.

Table 3. Pharmacokinetic Parameters in Patients 7.7 to 27 Years of Age
Pharmacokinetic Parameter | Week 1 Mean (SD) | Week 27 Mean (SD)
Cmax (mcg/mL) | 1.5 (0.6) | 1.1 (0.3)
AUC (min•mcg/mL) | 206 (87) | 169 (55)
t1/2 (min) | 44 (19) | 48 (21)
CL (mL/min/kg) | 3.0 (1.2) | 3.4 (1.0)
Vss (mL/kg) | 213 (82) | 254 (87)

Clinical Trial in Patients 7 Years and Younger

Idursulfase pharmacokinetics was evaluated in 27 patients with Hunter syndrome 16 months to 7.5 years of age who received ELAPRASE 0.5 mg/kg once weekly as a 3-hour infusion. The presence of anti-idursulfase antibody (Ab) was associated with a reduced systemic exposure of idursulfase. Eight of the 18 Ab-positive patients had no measurable idursulfase concentrations. An additional 9 Ab-positive patients had decreased Cmax, AUC, and t1/2 at Week 27 compared to Week 1 (Table 4). Idursulfase pharmacokinetics was similar between Week 1 and Week 27 in Ab-negative patients (Table 4).

Table 4. Pharmacokinetic Parameters in Patients 16 months to 7.5 Years of Age
 | Week 1 | Week 27
Pharmacokinetic Parameter | (N=27) All Patients Mean (SD) | Anti-idursulfase Antibodies (Ab) [Positive anti-idursulfase antibody (Ab) is defined as having at least one serum specimen with measurable antibody during study duration.]
Pharmacokinetic Parameter | (N=27) All Patients Mean (SD) | (n=9) Negative Ab Mean (SD) | (n=10 [Eight of 18 patients with positive Ab had no measurable concentrations at Week 27.]) Positive Ab Mean (SD)
Cmax (mcg/mL) | 1.33 (0.817) | 1.40 (0.389) | 0.706 (0.558)
AUC (min•mcg/mL) | 224 (76.9) [N=26] | 281 (81.8) | 122 (92.1) [N=9]
t1/2 (min) | 160 (69) | 134 (19) | 84 (46)
CL (mL/min/kg) | 2.4 (0.7) | 2.0 (0. 8) | 7.4 (6.0)
Vss (mL/kg) | 394 (423) | 272 (112) | 829 (636)

All patients with the complete gene deletion or large gene rearrangement genotype (n=8) developed Ab at Week 27. Five of these eight patients had no measurable idursulfase concentrations at Week 27, and three had a lower systemic exposure at Week 27 compared to Week 1.

13 NONCLINICAL TOXICOLOGY

13.1 Carcinogenesis, Mutagenesis, Impairment of Fertility

Long-term studies in animals to evaluate carcinogenic potential or studies to evaluate mutagenic potential have not been performed with ELAPRASE.

ELAPRASE at intravenous doses up to 5 mg/kg administered twice weekly (about 1.6 times the recommended human weekly dose based on body surface area) had no effect on fertility and reproductive performance in male rats.

14 CLINICAL STUDIES

14.1 Clinical Trials in Patients 5 Years and Older

The safety and efficacy of ELAPRASE were evaluated in a 53-week, randomized, double-blind, placebo-controlled clinical trial of 96 patients with Hunter syndrome. The trial included patients with deficiency in iduronate-2-sulfatase enzyme activity and a percent predicted forced vital capacity (%-predicted FVC) less than 80%. The age of patients ranged from 5 to 31 years. Patients received ELAPRASE 0.5 mg/kg once per week (n=32), ELAPRASE 0.5 mg/kg once every other week (n=32), or placebo (n=32).

The primary efficacy outcome assessment was a two-component composite score based on the sum of the ranks of the change from baseline to Week 53 in distance walked in six minutes (6-minute walk test) and the ranks of the change in %-predicted FVC. This two-component composite primary endpoint differed statistically significantly between the three groups, and the difference was greatest between the placebo group and the once weekly treatment group (once weekly ELAPRASE vs. placebo, p=0.0049).

Examination of the individual components of the composite score showed that, in the adjusted analysis, the weekly ELAPRASE-treated group experienced a 35 meter greater mean increase in the distance walked in six minutes compared to placebo. The changes in %-predicted FVC were not statistically significant (Table 5).

Table 5. Clinical Trial Results
 | ELAPRASE Weekly n=32 [One patient in the placebo group and one patient in the ELAPRASE group died before Week 53; imputation was by last observation carried forward in the intent-to-treat analysis.] |  |  | Placebo n=32 |  |  | ELAPRASE Once Weekly – Placebo
 | Baseline | Week 53 | Change [Change, calculated as Week 53 minus Baseline] | Baseline | Week 53 | Change | Difference in Change
Results from the 6-Minute Walk Test (Meters)
Mean ± SD | 392 ± 108 | 436 ± 138 | 44 ± 70 | 393 ± 106 | 400 ± 106 | 7 ± 54 | 37 ± 16 [Observed mean ± SE] 35 ± 14 [ANCOVA model based mean ± SE, adjusted for baseline disease severity, region, and age.] (p=0.01)
Median | 397 | 429 | 31 | 403 | 412 | -4
Percentiles (25th, 75th) | 316, 488 | 365, 536 | 0, 94 | 341, 469 | 361, 460 | -30, 31
Results from the Forced Vital Capacity Test (% of Predicted)
Mean ± SD | 55.3 ± 15.9 | 58.7 ± 19.3 | 3.4 ± 10.0 | 55.6 ± 12.3 | 56.3 ± 15.7 | 0.8 ± 9.6 | 2.7 ± 2.5 4.3 ± 2.3 (p=0.07)
Median | 54.9 | 59.2 | 2.1 | 57.4 | 54.6 | -2.5 | 2.7 ± 2.5 4.3 ± 2.3 (p=0.07)
Percentiles (25th, 75th) | 43.6, 69.3 | 44.4, 70.7 | -0.8, 9.5 | 46.9, 64.4 | 43.8, 67.5 | -5.4, 5.0

Pharmacodynamic assessments included urinary GAG levels and changes in liver and spleen size. Urinary GAG levels were elevated in all patients at baseline. Following 53 weeks of treatment, mean urinary GAG levels were reduced in the ELAPRASE once weekly group, although GAG levels still remained above the upper limit of normal in half of the ELAPRASE-treated patients. Urinary GAG levels remained elevated and essentially unchanged in the placebo group. Sustained reductions in both liver and spleen volumes were observed in the ELAPRASE once weekly group through Week 53 compared to placebo. There were essentially no changes in liver and spleen volumes in the placebo group.

Extension Trial

Patients who participated in the placebo-controlled trial were eligible to continue treatment in an open-label extension trial. During the extension trial, all patients received ELAPRASE 0.5mg/kg once weekly for 24 months.

Patients who were treated with ELAPRASE once weekly and every other week in the placebo-controlled trial demonstrated improvement in distance walked in the 6-minute walk test for an additional 8 months of treatment in the extension trial. There was no change in mean %-predicted FVC in all Hunter syndrome patients after 6 months of treatment in the extension trial; however, a slight decrease in mean %-predicted FVC was demonstrated through to month 24 of the extension trial. The long-term effect of ELAPRASE on pulmonary function in Hunter syndrome patients is unclear.

There were no further reductions in mean urinary GAG levels in patients initially treated with ELAPRASE once weekly; however, the patients treated with ELAPRASE every other week during the placebo-controlled trial experienced further reductions in mean urinary GAG levels after changing to a more frequent dosing regimen during the extension trial. The persistence of reduced urinary GAG levels did not correlate with the long term effect demonstrated by the 6-minute walk test distance or %-predicted FVC.

14.2 Clinical Trial in Patients 7 Years and Younger

A 53-week, open-label, multicenter, single-arm trial was conducted to assess the safety, pharmacokinetics, and pharmacodynamics of ELAPRASE 0.5 mg/kg once weekly in male Hunter syndrome patients aged 7 years and younger. Safety results demonstrated that patients with complete gene deletion or large gene rearrangement mutations are more likely to develop antibodies, including neutralizing antibodies, and to experience hypersensitivity reactions with ELAPRASE administration [see Adverse Reactions (6.1, 6.2)]. In patients who remained antibody negative, the pharmacokinetic profile, reduction in urinary GAG excretion levels, and reduction in spleen volume were similar to those of adults and children 5 years and older. In patients who were persistently antibody positive, the presence of anti-idursulfase antibody was associated with reduced systemic exposure of idursulfase and a less pronounced decrease in urinary GAG levels [see Clinical Pharmacology (12.2, 12.3)].

16 HOW SUPPLIED/STORAGE AND HANDLING

ELAPRASE is supplied as a sterile injection in a 5 mL Type I glass vial. The vials are closed with a butyl rubber stopper with fluororesin coating and an aluminum overseal with a blue flip-off plastic cap.

Each carton contains a single vial NDC 54092-700-01

STORAGE AND HANDLING

Store ELAPRASE vials in the carton at 2°C to 8°C (36°F to 46°F) to protect from light. Do not freeze or shake. Do not use ELAPRASE after the expiration date on the vial.

17 PATIENT COUNSELING INFORMATION

Information for Patients

Patients should be advised that life-threatening anaphylactic reactions have occurred in some patients during and up to 24 hours after ELAPRASE therapy. Patients who have experienced anaphylactic reactions may require prolonged observation. Patients with compromised respiratory function or acute respiratory disease may be at risk of serious acute exacerbation of their respiratory compromise due to hypersensitivity reactions.

A Hunter Outcome Survey has been established in order to understand better the variability and progression of Hunter syndrome (MPS II) in the population as a whole, and to monitor and evaluate long-term treatment effects of ELAPRASE. Patients and their physicians are encouraged to participate in this program. For more information, call Takeda Pharmaceuticals at 1-877-825-3327.

Manufactured by:

Takeda Pharmaceuticals U.S.A., Inc.
Cambridge, MA 02142
US License Number: 1898

ELAPRASE and are registered trademarks of Shire Human Genetic Therapies, Inc.

©2025 Takeda Pharmaceutical Company Limited. All rights reserved.

PRINCIPAL DISPLAY PANEL - 6 mg/3 mL Vial Carton

elaprase®
(idursulfase)
injection

6 mg/3 mL
(2 mg/mL)

Single Use Vial,
Discard Unused Portion

Must be diluted for
intravenous infusion

Rx Only

Takeda